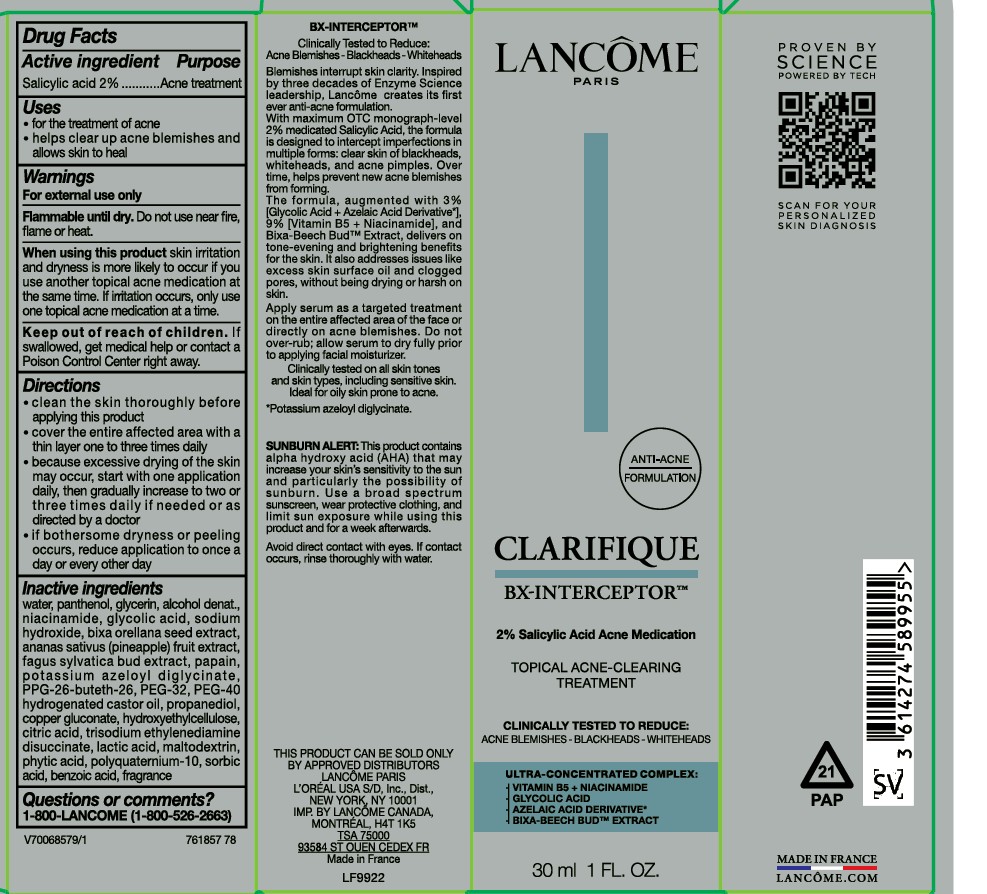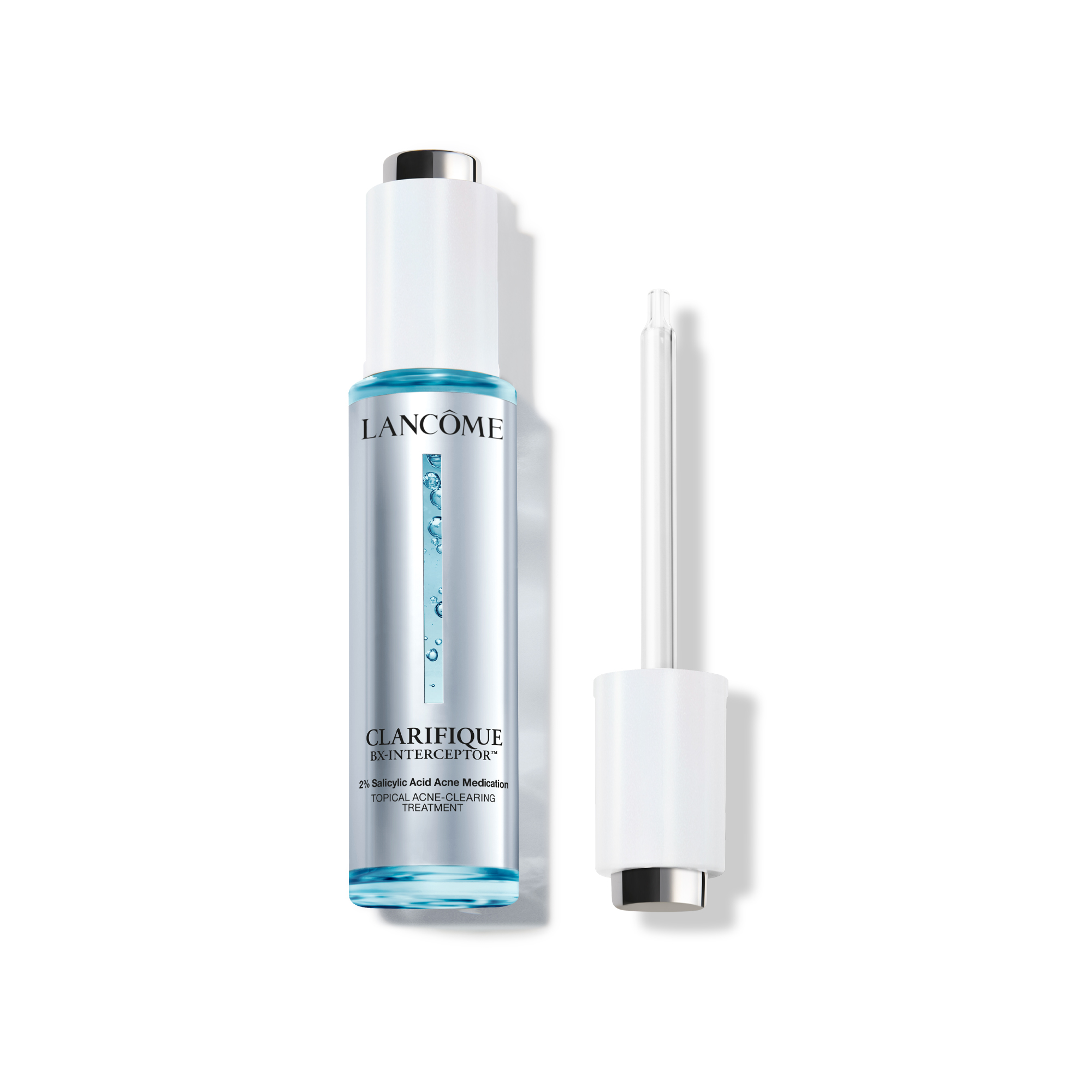 DRUG LABEL: Lancome Paris Clarifique BX-Interceptor Topical Acne Clearing Treatment
NDC: 82046-955 | Form: LIQUID
Manufacturer: L’Oreal USA Products Inc
Category: otc | Type: HUMAN OTC DRUG LABEL
Date: 20260302

ACTIVE INGREDIENTS: SALICYLIC ACID 20 mg/1 mL
INACTIVE INGREDIENTS: WATER; PANTHENOL; GLYCERIN; ALCOHOL; NIACINAMIDE; GLYCOLIC ACID; SODIUM HYDROXIDE; BIXA ORELLANA SEED; PINEAPPLE; FAGUS SYLVATICA FLOWER BUD; PAPAIN; POTASSIUM AZELOYL DIGLYCINATE; PPG-26-BUTETH-26; PEG-32; PEG-40 HYDROGENATED CASTOR OIL; PROPANEDIOL; COPPER GLUCONATE; HYDROXYETHYLCELLULOSE; CITRIC ACID; TRISODIUM ETHYLENEDIAMINE DISUCCINATE; LACTIC ACID; MALTODEXTRIN; PHYTIC ACID; POLYQUATERNIUM-10 (400 MPA.S AT 2%); SORBIC ACID; BENZOIC ACID

Drug Facts

Active ingredient

Salicylic acid 2%

Purpose

Acne treatment

Uses

- for the treatment of acne
- helps clear up acne blemishes and allows skin to heal

Warnings

For external use only.

Flammable until dry.

Do not use near fire, flame or heat.

When using this product

skin irritation and dryness is more likely to occur if you use another topical acne medication at the same time. If irritation occurs, only use one topical acne medication at a time.

Keep out of reach of children.

If swallowed, get medical help or contact a Poison Control Center right away.

Directions

- clean the skin thoroughly before applying this product
- cover the entire affected area with a thin layer one to three times daily
- because excessive drying of the skin may occur, start with one application daily, then gradually increase to two or three times daily if needed or as directed by a doctor
- if bothersome dryness or peeling occurs, reduce application to once a day or every other day

Inactive ingredients

water, panthenol, glycerin, alcohol denat., niacinamide, glycolic acid, sodium hydroxide, bixa orellana seed extract, ananas sativus (pineapple) fruit extract, fagus sylvatica bud extract, papain, potassium azeloyl diglycinate, PPG-26-buteth-26, PEG-32, PEG-40 hydrogenated castor oil, propanediol, copper gluconate, hydroxyethylcellulose, citric acid, trisodium ethylenediamine disuccinate, lactic acid, maltodextrin, phytic acid, polyquaternium-10, sorbic acid, benzoic acid, fragrance

Questions or comments?

1-800-LANCOME (1-800-526-2663)